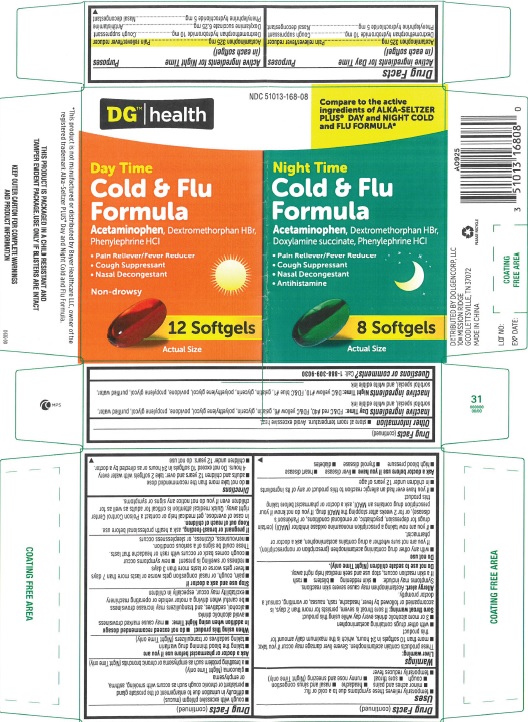 DRUG LABEL: DG Day Time Cold and Flu Formula and Night Time Cold and Flu Formula
NDC: 51013-168 | Form: KIT | Route: ORAL
Manufacturer: PuraCap Pharmaceutical LLC
Category: otc | Type: HUMAN OTC DRUG LABEL
Date: 20241122

ACTIVE INGREDIENTS: ACETAMINOPHEN 325 mg/1 1; DEXTROMETHORPHAN HYDROBROMIDE 10 mg/1 1; PHENYLEPHRINE HYDROCHLORIDE 5 mg/1 1; ACETAMINOPHEN 325 mg/1 1; DEXTROMETHORPHAN HYDROBROMIDE 10 mg/1 1; PHENYLEPHRINE HYDROCHLORIDE 5 mg/1 1; DOXYLAMINE SUCCINATE 6.25 mg/1 1
INACTIVE INGREDIENTS: FD&C RED NO. 40; FD&C YELLOW NO. 6; GELATIN; GLYCERIN; POLYETHYLENE GLYCOL, UNSPECIFIED; POVIDONE; PROPYLENE GLYCOL; WATER; SORBITOL; D&C YELLOW NO. 10; FD&C BLUE NO. 1; GELATIN; GLYCERIN; POLYETHYLENE GLYCOL, UNSPECIFIED; POVIDONE; PROPYLENE GLYCOL; WATER; SORBITOL

Day Time Cold & Flu Formula and Night Time Cold & Flu Formula

Active ingredients (in each softgel)

Active ingredients for Day Time (in each softgel)

Acetaminophen 325 mg
Dextromethorphan hydrobromide 10 mg
Phenylephrine hydrochloride 5 mg

Active ingredients for Night Time (in each softgel)

Acetaminophen 325 mg
Dextromethorphan hydrobromide 10 mg
Doxylamine succinate 6.25 mg
Phenylephrine hydrochloride 5 mg

Purposes

DG Day Time Cold & Flu Formula

Pain reliever/fever reducer

Cough suppressant

Nasal decongestant

DG Night Time Cold & Flu Formula

Pain reliever/fever reducer

Cough suppressant

Antihistamine

Nasal decongestant

Uses

- temporarily relieves these symptoms due to a cold or flu:
  - minor aches and pains
  - headache
  - nasal and sinus congestion
  - cough
  - sore throat
  - runny nose and sneezing (Night Time only)
- temporarily reduces fever

Warnings

Liver warning

These products contain acetaminophen. Severe liver damage may occur if you take

- more than 10 softgels in 24 hours, which is the maximum daily amount for this product
- with other drugs containing acetaminophen
- 3 or more alcoholic drinks every day while using this product

Sore throat warning

If sore throat is severe, persists for more than 2 days, is accompanied or followed by fever, headache, rash, nausea, or vomiting, consult a doctor promptly.

Allergy alert:Acetaminophen may cause severe skin reactions. Symptoms may include:

- skin reddening
- blisters
- rash
  If a skin reaction occurs, stop use and seek medical help right away.
  Do not use to sedate children(Night Time only).

Do not use

- with any other drug containing acetaminophen (prescription or nonprescription). If you are not sure whether a drug contains acetaminophen, ask a doctor or pharmacist.
- if you are now taking a prescription monoamine oxidase inhibitor (MAOI) (certain drugs for depression, psychiatric, or emotional conditions, or Parkinson's disease), or for 2 weeks after stopping the MAOI drug. If you do not know if your prescription drug contains an MAOI, ask a doctor or pharmacist before taking this product.
- if you have ever had an allergic reaction to this product or any of its ingredients
- in children under 12 years of age

Ask a doctor before use if you have

- liver disease
- heart disease
- high blood pressure
- thyroid disease
- diabetes
- cough with excessive phlegm (mucus)
- difficulty in urination due to enlargement of the prostate gland
- persistent or chronic cough such as occurs with smoking, asthma, or emphysema
- glaucoma (Night Time only)
- a breathing problem such as emphysema or chronic bronchitis (Night Time only)

Ask a doctor or pharmacist before use if you are

- taking the blood thinning drug warfarin
- taking sedatives or tranquilizers (Night Time only)

When using this product

- do not exceed recommended dosage

In addition when using Night Time

- may cause marked drowsiness
- avoid alcoholic drinks
- alcohol, sedatives, and tranquilizers may increase drowsiness
- be careful when driving a motor vehicle or operating machinery
- excitability may occur, especially in children

Stop use and ask a doctor if

- pain, cough, or nasal congestion gets worse or lasts more than 7 days
- fever gets worse or lasts more than 3 days
- redness or swelling is present
- new symptoms occur
- cough comes back or occurs with rash or headache that lasts.

These could be signs of a serious condition.

- nervousness, dizziness, or sleeplessness occurs

If pregnant or breast-feeding,

ask a health professional before use.

Keep out of reach of children.

In case of overdose, get medical help or contact a Poison Control Center right away. Quick medical attention is critical for adults as well as for children even if you do not notice any signs or symptoms.

Directions

- do not take more than the recommended dose
- adults and children 12 years and over: take 2 softgels with water every 4 hours. Do not exceed 10 softgels in 24 hours or as directed by a doctor.
- children under 12 years: do not use

Other information

- store at room temperature. Avoid excessive heat.

Inactive ingredients (Day Time)

FD&C red #40, FD&C yellow #6, gelatin, glycerin, polyethylene glycol, povidone, propylene glycol, purified water, sorbitol special, and white edible ink

Inactive ingredients (Night Time)

D&C yellow #10, FD&C blue #1, gelatin, glycerin, polyethylene glycol, povidone, propylene glycol, purified water, sorbitol special, and white edible ink

Questions or comments?

Call: 1-888-309-9030

Principal Display Panel - Carton Label

DG Day and Night Cold and Flu Formula

NDC 51013-168-08

*Compare to the active ingredients in Alka-Seltzer PLUS® Day and Night Cold and Flu Formula